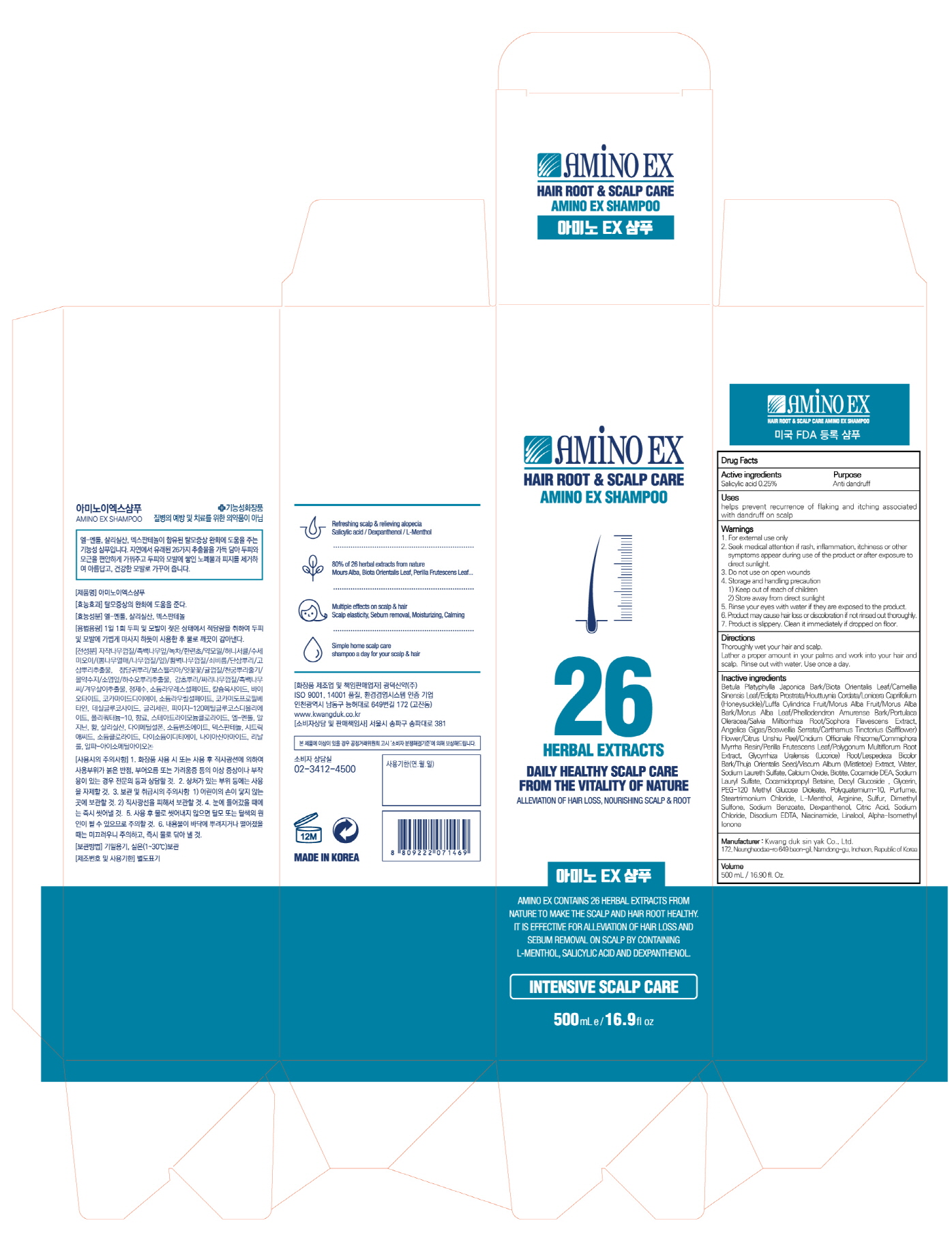 DRUG LABEL: AMINO EX
NDC: 71838-0010 | Form: SHAMPOO
Manufacturer: Kwang Duk Sin Yak Co., Ltd.
Category: otc | Type: HUMAN OTC DRUG LABEL
Date: 20200609

ACTIVE INGREDIENTS: SALICYLIC ACID 0.25 g/100 mL
INACTIVE INGREDIENTS: WATER; LEVOMENTHOL

ACTIVE INGREDIENT

Salicylic acid 0.25%

INACTIVE INGREDIENT

Betula Platyphylla Japonica Bark/Biota Orientalis Leaf/Camellia Sinensis Leaf/EcliptaProstrata/Houttuynia Cordata/Lonicera Caprifolium (Honeysuckle)/Luffa Cylindrica Fruit/MorusAlba Fruit/Morus Alba Bark/Morus Alba Leaf/Phellodendron Amurense Bark/PortulacaOleracea/Salvia Miltiorrhiza Root/Sophora Flavescens Extract, Angelica Gigas/Boswellia Serrata/Carthamus Tinctorius (Safflower) Flower/Citrus UnshiuPeel/Cnidium Officinale Rhizome/Commiphora Myrrha Resin/Perilla Frutescens Leaf/PolygonumMultiflorum Root Extract, Glycyrrhiza Uralensis (Licorice) Root/Lespedeza Bicolor Bark/Thuja Orientalis Seed/ViscumAlbum (Mistletoe) Extract, Water, , Sodium Laureth Sulfate, Calcium Oxide, Biotite, Cocamide DEA, Sodium Lauryl Sulfate, Cocamidopropyl Betaine, Decyl Glucoside, Glycerin, PEG-120 Methyl Glucose Dioleate, Polyquaternium-10, Purfume, Steartrimonium Chloride, L-Menthol, Arginine, Sulfur, Salicylic Acid, Dimethyl Sulfone, Sodium Benzoate

PURPOSE

helps prevent recurrence of flaking and itching associated with dandruff on scalp

WARNINGS

- For external use only
- Seek medical attention if rash, inflammation, itchiness or other symptoms appear during use of the product or after exposure to direct sunlight.
- Do not use on open wounds
- Storage and handling precaution

1. Keep out of reach of children
2. Store away from direct sunlight

- Rinse your eyes with water if they are exposed to the product.
- Product may cause hair loss or discoloration if not rinsed out thoroughly.
- Product is slippery. Clean it immediately if dropped on floor.

KEEP OUT OF REACH OF CHILDREN

INDICATIONS AND USAGE

For external use only

DOSAGE AND ADMINISTRATION

Thoroughly wet your hair and scalp.
Lather a proper amount in your palms and work into your hair and scalp. Rinse out with water. Use once a day.